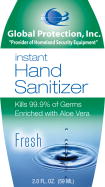 DRUG LABEL: Instant Hand Sanitizer
NDC: 50225-355 | Form: GEL
Manufacturer: Global Protection USA, Inc.
Category: otc | Type: HUMAN OTC DRUG LABEL
Date: 20100106

ACTIVE INGREDIENTS: Alcohol 60 g/1 mL
INACTIVE INGREDIENTS: Aloe; D&C Green no. 5; D&C Yellow no. 10; water

Instant Hand Sanitizer

Active Ingredient

Ethyl Alcohol 66.5%

Purpose

Antiseptic

Uses

- for handwashing to decrease bacteria on skin without soap and water
- recommended for repeated use

Warnings

For external use only

Flammable, keep away from fire or flame

Do not use in the eyes. If this happens, rinse thoroughly with water

Stop use and ask a doctor if irritation and redness develop and persists for more than 72 hours

Keep out of reach of children

If ingested get medical help or contact a Poison Control Center right away

Directions

- wet hands thoroughly with product
- allow to dry without wiping
- children under 6 should be supervised while using this product

INACTIVE INGREDIENT

Inactive ingredients aloe vera, carbomer, D&C green #5, D&C yellow #10, fragrance, purified water, triethanolamine

Distributed by
Global Protection USA, Inc.
West Berlin, NJ 08091
800-957-8955

PACKAGE LABEL - PRINCIPAL DISPLAY PANEL – BOTTLE

Global Protection, Inc. “Provider of Homeland Security Equipment”

Instant Hand Sanitizer

Kills 99.9% of Germs

Enriched with Aloe Vera

2 Fl. oz. (59ML)